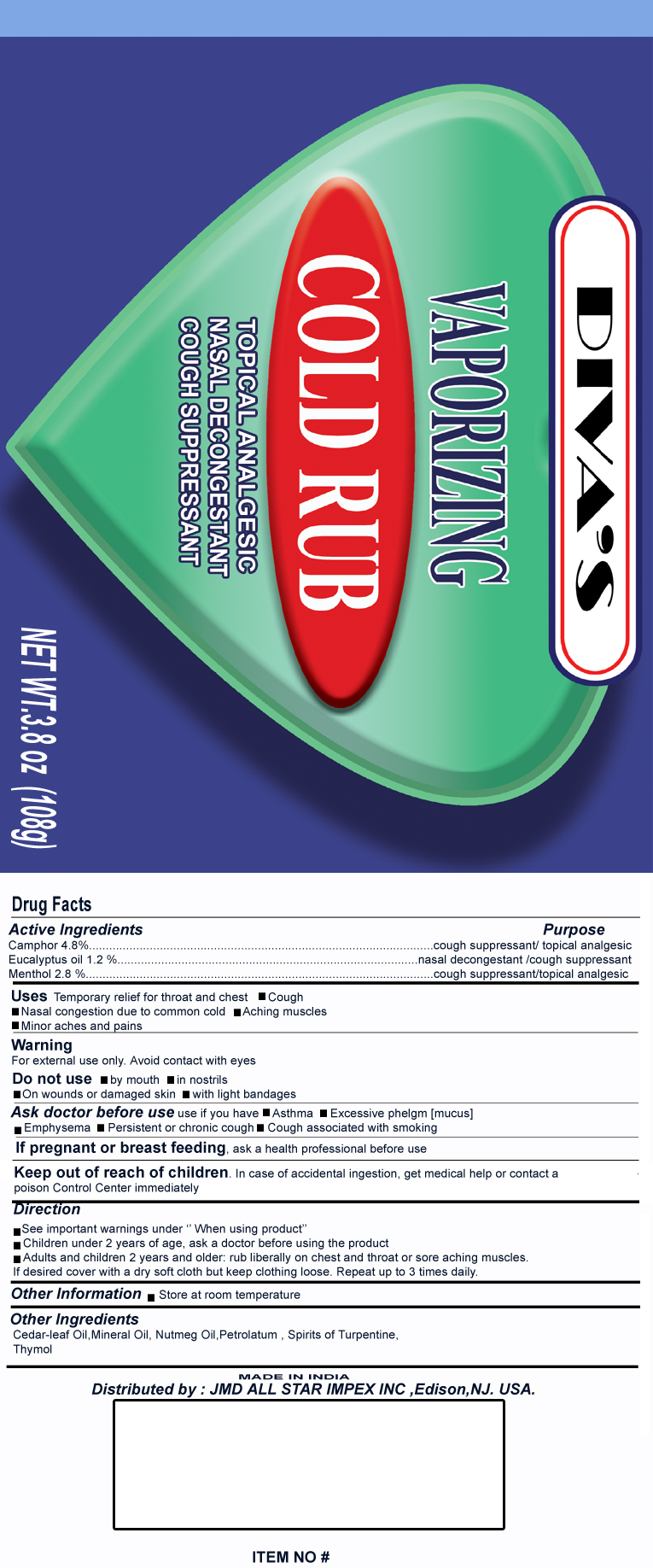 DRUG LABEL: Cold Rub
NDC: 51444-001 | Form: OINTMENT
Manufacturer: JMD All Star Impex Inc.
Category: otc | Type: HUMAN OTC DRUG LABEL
Date: 20100530

ACTIVE INGREDIENTS: CAMPHOR (NATURAL) 4.8 g/100 g; EUCALYPTUS OIL 1.2 g/100 g; MENTHOL 2.8 g/100 g
INACTIVE INGREDIENTS: CEDAR LEAF OIL; NUTMEG; PETROLATUM; THYMOL; TURPENTINE

Active Ingredients
Camphor 4.8%
Eucalyptus oil 1.2%
Menthol 2.8%

PURPOSE

cough suppressant/topical analgesic
nasal decongestant/cough suppressant
cough suppressant/topical analgesic

Uses

Temporarily relief for throat and chest

- Cough
- Nasal congestion due to common cold
- Aching muscles
- Minor aches and pains

Warning
For external use only. Avoid contact with eyes.

Do not use

- by mouth
- in nostrils
- on wounds or damaged skin
- with light bandages

Ask a doctor before use if you have

- Asthma
- Excessive phlegm (mucus)
- Emphysema
- Persistent or chronic cough
- Cough associated with smoking

PREGNANCY OR BREAST FEEDING

If pregnant or breast feeding, ask a health professional before use

Keep out of reach of children. If case of accidental ingestion, get medical help or contact a Poison Control Center immediately.

Directions

- See important warnings under "When using product"
- Children under 2 years of age, ask a doctor before using the product
- Adults and children 2 years of age and older: rub a thick layer chest and throat or sore aching muscles. If desired loosely cover with a soft cloth but keep clothing loose. Repeat up to 3 times daily

Other Information

- Store at room temperature

INACTIVE INGREDIENT

Other Ingredients
Cedar leaf Oil, Mineral Oil, Nutmeg Oil, Petrolatum, Spirits of Turpentine, Thymol

Package Label